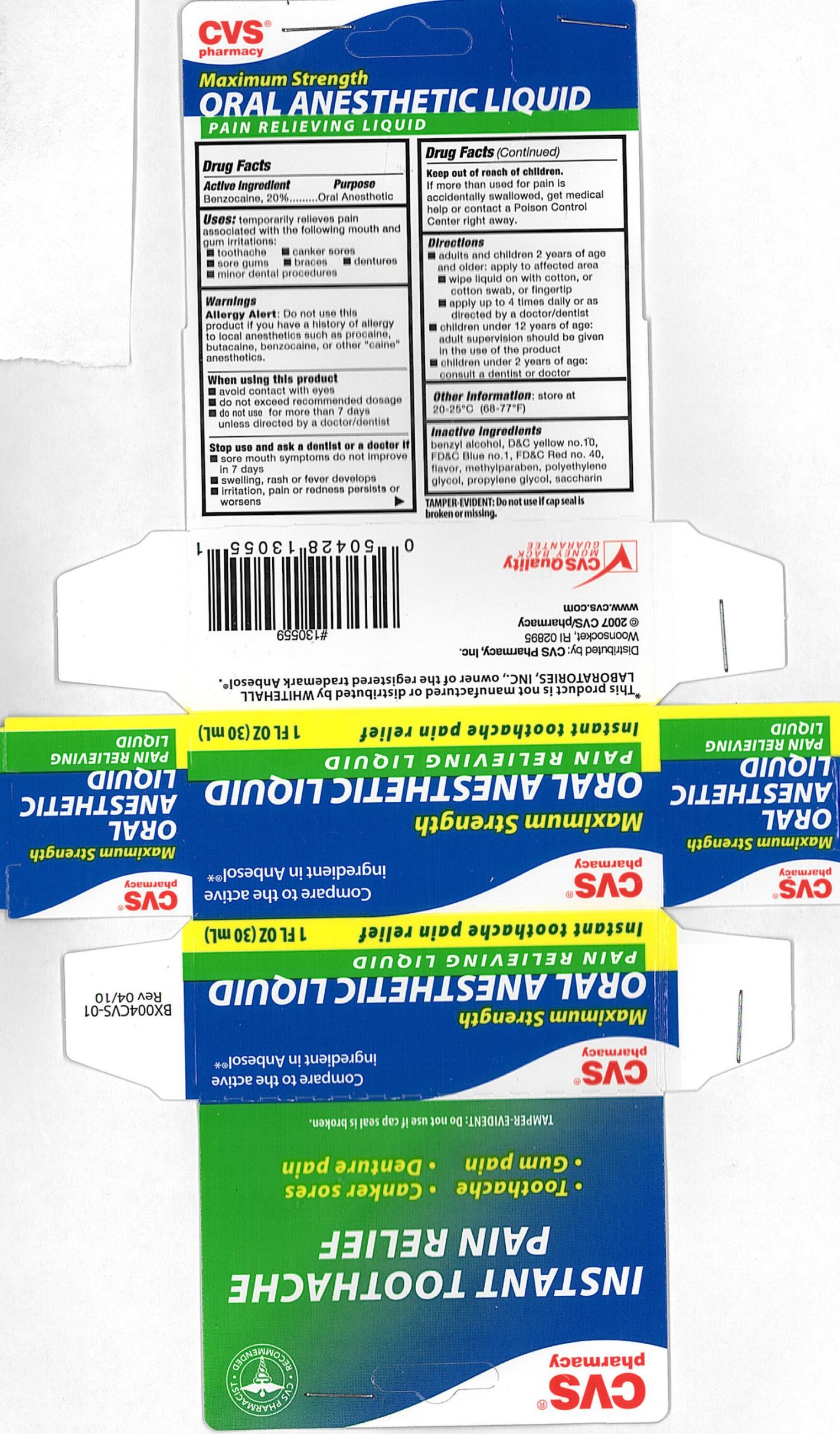 DRUG LABEL: CVS Oral Anesthetic
NDC: 59779-186 | Form: LIQUID
Manufacturer: CVS Pharmacy
Category: otc | Type: HUMAN OTC DRUG LABEL
Date: 20100708

ACTIVE INGREDIENTS: BENZOCAINE 200 mg/1 mL
INACTIVE INGREDIENTS: BENZYL ALCOHOL; D&C YELLOW NO. 10; FD&C RED NO. 40; SPEARMINT OIL; PEPPERMINT OIL; METHYLPARABEN; POLYETHYLENE GLYCOL 400; PROPYLENE GLYCOL; SACCHARIN

drug facts

Active ingredient Purpose
Benzocaine, 20%........................................Oral Anesthetic

Uses
- temporary relieves pain associated with the following mouth and gum irritations:
- toothache - canker sores - sore gums - braces - dentures
- minor dental procedures

Keep out of reach of children. If more than is used for pain is accidentally
swallowed, get medical help or contact a Poison Control Center right away.

Uses
- temporary relieves pain associated with the following mouth and gum irritations:
- toothache - canker sores - sore gums - braces - dentures
- minor dental procedures

Warnings
Allergy Alert: Do not use this product if you have a history of allergy to local anesthetics
such as procaine, butacaine, benzocaine or other "caine" anesthetics.
When using this product
- avoid contact with eyes
- do not exceed recommended dosage
- do not use for more than 7 days unless directed by a doctor/dentist
Stop use and ask a dentist or a doctor if
- sore mouth symptoms do not improve in 7 days
- swelling, rash or fever develops
- irritation, pain or redness persists or worsens
Keep out of reach of children.If more then used for pain is accidentally swallowed,
get medical help or contact a Poison Control Center right away.

Directions
- Adults and children 2 years of age and older: apply to the affected area
- wipe liquid on with cotton, or cotton swab, or fingertip
- apply up to 4 times daily or as recommended by a doctor/dentist
- Children under 12 years of age: adult supervision should be given in the use of this product
- children under 2 years of age: consult a dentist or doctor

Inactive Ingredients
benzyl alcohol, D and C Yellow no 10, FD and C Blue no 1, FD and C Red no 40,
flavor, methylparaben, polyethylene glycol, propylene glycol, saccharin